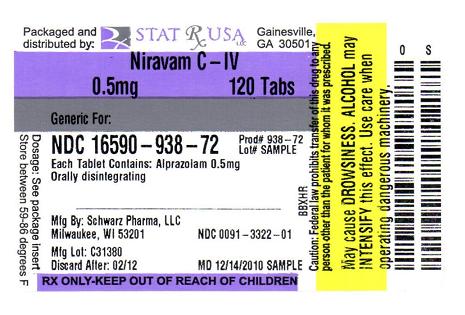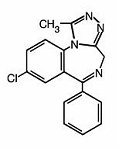 DRUG LABEL: NIRAVAM
NDC: 16590-938 | Form: TABLET, ORALLY DISINTEGRATING
Manufacturer: STAT RX USA LLC
Category: prescription | Type: HUMAN PRESCRIPTION DRUG LABEL
Date: 20110419
DEA Schedule: CIV

ACTIVE INGREDIENTS: ALPRAZOLAM 0.5 mg/1 1
INACTIVE INGREDIENTS: SILICON DIOXIDE; STARCH, CORN; CROSPOVIDONE; MAGNESIUM STEARATE; MANNITOL; CELLULOSE, MICROCRYSTALLINE; SUCRALOSE; SUCROSE; FERRIC OXIDE YELLOW

NIRAVAM®
(alprazolam orally
disintegrating tablets)

Rx Only
PC4714D
Rev. 12/06
80-03019-904
CIV

DESCRIPTION

NIRAVAM® (alprazolam orally disintegrating tablets) contains alprazolam which is a triazolo analog of the 1,4 benzodiazepine class of central nervous system-active compounds. NIRAVAM® is an orally administered formulation of alprazolam which rapidly disintegrates on the tongue and does not require water to aid dissolution or swallowing.

The chemical name of alprazolam is 8-Chloro-1-methyl-6-phenyl-4H-s-triazolo [4,3-α] [1,4] benzodiazepine. The empirical formula is C17H13CIN4 and the molecular weight is 308.76. The structural formula is:

Alprazolam is a white crystalline powder, which is soluble in methanol or ethanol but which has no appreciable solubility in water at physiological pH.

Each orally disintegrating tablet contains either 0.25, 0.5, 1 or 2 mg of alprazolam and the following inactive ingredients: colloidal silicon dioxide, corn starch, crospovidone, magnesium stearate, mannitol, methacrylic acid copolymer, microcrystalline cellulose, natural and artificial orange flavor, sucralose and sucrose. In addition, the 0.25 mg and 0.5 mg tablets contain yellow iron oxide.

CLINICAL PHARMACOLOGY

Pharmacodynamics

CNS agents of the 1,4 benzodiazepine class presumably exert their effects by binding at stereo specific receptors at several sites within the central nervous system. Their exact mechanism of action is unknown. Clinically, all benzodiazepines cause a dose-related central nervous system depressant activity varying from mild impairment of task performance to hypnosis.

Pharmacokinetics

Absorption

Following oral administration, alprazolam is readily absorbed. The peak plasma concentration is reached about 1.5 to 2 hours after administration of NIRAVAM® given with or without water. When taken with water, mean Tmax occurs about 15 minutes earlier than when taken without water with no change in Cmax or AUC. Plasma levels are proportional to the dose given; over the dose range of 0.5 to 3.0 mg, peak levels of 8.0 to 37 ng/mL are observed. The elimination half-life of alprazolam is approximately 12.5 hours (range 7.9-19.2 hours) after administration of NIRAVAM® in healthy adults.

Food decreased the mean Cmax by about 25% and increased the mean Tmax by 2 hours from
2.2 hours to 4.4 hours after the ingestion of a high-fat meal. Food did not affect the extent of absorption (AUC) or the elimination half-life.

Distribution

In vitro, alprazolam is bound (80 percent) to human serum protein. Serum albumin accounts for the majority of the binding.

Metabolism/Elimination

Alprazolam is extensively metabolized in humans, primarily by cytochrome P450 3A4 (CYP3A4), to two major metabolites in the plasma: 4-hydroxyalprazolam and α-hydroxyalprazolam. A benzophenone derived from alprazolam is also found in humans. Their half-lives appear to be similar to that of alprazolam. The plasma concentrations of 4-hydroxyalprazolam and α-hydroxyalprazolam relative to unchanged alprazolam concentration were always less than 4%. The reported relative potencies in benzodiazepine receptor binding experiments and in animal models of induced seizure inhibition are 0.20 and 0.66, respectively, for 4-hydroxyalprazolam and α-hydroxyalprazolam. Such low concentrations and the lesser potencies of 4-hydroxyalprazolam and α-hydroxyalprazolam suggest that they are unlikely to contribute much to the pharmacological effects of alprazolam. The benzophenone metabolite is essentially inactive.

Alprazolam and its metabolites are excreted primarily in the urine.

Special Populations

Changes in the absorption, distribution, metabolism and excretion of benzodiazepines have been reported in a variety of disease states including alcoholism, impaired hepatic function and impaired renal function. Changes have also been demonstrated in geriatric patients. A mean half-life of alprazolam of 16.3 hours has been observed in healthy elderly subjects (range: 9.0 - 26.9 hours, n=16) compared to 11.0 hours (range: 6.3 - 15.8 hours, n=16) in healthy adult subjects. In patients with alcoholic liver disease, the half-life of alprazolam ranged between 5.8 and 65.3 hours (mean: 19.7 hours, n=17) as compared to between 6.3 and 26.9 hours (mean=11.4 hours, n=17) in healthy subjects. In an obese group of subjects, the half-life of alprazolam ranged between 9.9 and 40.4 hours (mean=21.8 hours, n=12) as compared to between 6.3 and 15.8 hours (mean=10.6 hours, n=12) in healthy subjects.

Because of its similarity to other benzodiazepines, it is assumed that alprazolam undergoes transplacental passage and that it is excreted in human milk.

Race — Maximal concentrations and half-life of alprazolam are approximately 15% and 25% higher in Asians compared to Caucasians.

Pediatrics — The pharmacokinetics of alprazolam in pediatric patients have not been studied.

Gender — Gender has no effect on the pharmacokinetics of alprazolam.

Cigarette Smoking — Alprazolam concentrations may be reduced by up to 50% in smokers compared to non-smokers.

Drug-Drug Interactions

Alprazolam is primarily eliminated by metabolism via cytochrome P450 3A (CYP3A). Most of the interactions that have been documented with alprazolam are with drugs that inhibit or induce CYP3A4.

Compounds that are potent inhibitors of CYP3A would be expected to increase plasma alprazolam concentrations. Drug products that have been studied in vivo, along with their effect on increasing alprazolam AUC, are as follows: ketoconazole, 3.98 fold; itraconazole, 2.70 fold; nefazodone, 1.98 fold; fluvoxamine, 1.96 fold; and erythromycin, 1.61 fold (see CONTRAINDICATIONS, WARNINGS, and PRECAUTIONS–Drug Interactions).

CYP3A inducers would be expected to decrease alprazolam concentrations and this has been observed in vivo. The oral clearance of alprazolam (given in a 0.8 mg single dose) was increased from 0.90 ± 0.21 mL/min/kg to 2.13 ± 0.54 mL/min/kg and the elimination t1/2 was shortened (from 17.1 ± 4.9 to 7.7 ± 1.7 h) following administration of 300 mg/day carbamazepine for
10 days (see PRECAUTIONS–Drug Interactions). However, the carbamazepine dose used in this study was fairly low compared to the recommended doses (1000 - 1200 mg/day); the effect at usual carbamazepine doses is unknown.

The ability of alprazolam to induce or inhibit human hepatic enzyme systems has not been determined. However, this is not a property of benzodiazepines in general. Further, alprazolam did not affect the prothrombin or plasma warfarin levels in male volunteers administered sodium warfarin orally.

CLINICAL STUDIES

Anxiety Disorders

Alprazolam was compared to placebo in double blind clinical studies (doses up to 4 mg/day) in patients with a diagnosis of anxiety or anxiety with associated depressive symptomatology. Alprazolam was significantly better than placebo at each of the evaluation periods of these
4-week studies as judged by the following psychometric instruments: Physician's Global Impressions, Hamilton Anxiety Rating Scale, Target Symptoms, Patient's Global Impressions and Self-Rating Symptom Scale.

Panic Disorder

Support for the effectiveness of alprazolam in the treatment of panic disorder came from three short-term, placebo-controlled studies (up to 10 weeks) in patients with diagnoses closely corresponding to DSM-III-R criteria for panic disorder.

The average dose of alprazolam was 5 - 6 mg/day in two of the studies, and the doses of alprazolam were fixed at 2 and 6 mg/day in the third study. In all three studies, alprazolam was superior to placebo on a variable defined as "the number of patients with zero panic attacks" (range, 37 - 83% met this criterion), as well as on a global improvement score. In two of the three studies, alprazolam was superior to placebo on a variable defined as "change from baseline on the number of panic attacks per week" (range, 3.3 - 5.2), and also on a phobia rating scale. A subgroup of patients who were improved on alprazolam during short-term treatment in one of these trials was continued on an open basis up to 8 months, without apparent loss of benefit.

INDICATIONS AND USAGE

Anxiety Disorders

NIRAVAM® is indicated for the management of anxiety disorder (a condition corresponding most closely to the APA Diagnostic and Statistical Manual [DSM-III-R] diagnosis of generalized anxiety disorder) or the short-term relief of symptoms of anxiety. Anxiety or tension associated with the stress of everyday life usually does not require treatment with an anxiolytic.

Generalized anxiety disorder is characterized by unrealistic or excessive anxiety and worry (apprehensive expectation) about two or more life circumstances, for a period of 6 months or longer, during which the person has been bothered more days than not by these concerns. At least 6 of the following 18 symptoms are often present in these patients: Motor Tension (trembling, twitching, or feeling shaky; muscle tension, aches, or soreness; restlessness; easy fatigability); Autonomic Hyperactivity (shortness of breath or smothering sensations; palpitations or accelerated heart rate; sweating, or cold clammy hands; dry mouth; dizziness or lightheadedness; nausea, diarrhea, or other abdominal distress; flushes or chills; frequent urination; trouble swallowing or 'lump in throat'); Vigilance and Scanning (feeling keyed up or on edge; exaggerated startle response; difficulty concentrating or 'mind going blank' because of anxiety; trouble falling or staying asleep; irritability). These symptoms must not be secondary to another psychiatric disorder or caused by some organic factor.

Anxiety associated with depression is responsive to alprazolam.

Panic Disorder

NIRAVAM® is also indicated for the treatment of panic disorder, with or without agoraphobia.

Studies supporting this claim were conducted in patients whose diagnoses corresponded closely to the DSM-III-R/IV criteria for panic disorder (see CLINICAL STUDIES).

Panic disorder (DSM-IV) is characterized by recurrent unexpected panic attacks, ie, a discrete period of intense fear or discomfort in which four (or more) of the following symptoms develop abruptly and reach a peak within 10 minutes: (1) palpitations, pounding heart, or accelerated heart rate; (2) sweating; (3) trembling or shaking; (4) sensations of shortness of breath or smothering; (5) feeling of choking; (6) chest pain or discomfort; (7) nausea or abdominal distress; (8) feeling dizzy, unsteady, lightheaded, or faint; (9) derealization (feelings of unreality) or depersonalization (being detached from oneself); (10) fear of losing control; (11) fear of dying; (12) paresthesias (numbness or tingling sensations); (13) chills or hot flushes.

Demonstrations of the effectiveness of alprazolam by systematic clinical study are limited to
4 months duration for anxiety disorder and 4 to 10 weeks duration for panic disorder; however, patients with panic disorder have been treated on an open basis for up to 8 months without apparent loss of benefit. The physician should periodically reassess the usefulness of the drug for the individual patient.

CONTRAINDICATIONS

NIRAVAM® is contraindicated in patients with known sensitivity to this drug or other benzodiazepines. NIRAVAM® may be used in patients with open angle glaucoma who are receiving appropriate therapy, but is contraindicated in patients with acute narrow angle glaucoma.

NIRAVAM® is contraindicated with ketoconazole and itraconazole, since these medications significantly impair the oxidative metabolism mediated by cytochrome P450 3A (CYP3A) (see CLINICAL PHARMACOLOGY, WARNINGS and PRECAUTIONS–Drug Interactions).

WARNINGS

Dependence and Withdrawal Reactions, Including Seizures

Certain adverse clinical events, some life-threatening, are a direct consequence of physical dependence to alprazolam. These include a spectrum of withdrawal symptoms; the most important is seizure (see DRUG ABUSE AND DEPENDENCE). Even after relatively short-term use at the doses recommended for the treatment of transient anxiety and anxiety disorder
(ie, 0.75 to 4.0 mg per day), there is some risk of dependence. Spontaneous reporting system data suggest that the risk of dependence and its severity appear to be greater in patients treated with doses greater than 4 mg/day and for long periods (more than 12 weeks). However, in a controlled postmarketing discontinuation study of panic disorder patients, the duration of treatment
(3 months compared to 6 months) had no effect on the ability of patients to taper to zero dose. In contrast, patients treated with doses of alprazolam greater than 4 mg/day had more difficulty tapering to zero dose than those treated with less than 4 mg/day.

The importance of dose and the risks of alprazolam as a treatment for panic disorder

Because the management of panic disorder often requires the use of average daily doses of alprazolam above 4 mg, the risk of dependence among panic disorder patients may be higher than that among those treated for less severe anxiety. Experience in randomized placebo-controlled discontinuation studies of patients with panic disorder showed a high rate of rebound and withdrawal symptoms in patients treated with alprazolam compared to placebo-treated patients.

Relapse or return of illness was defined as a return of symptoms characteristic of panic disorder (primarily panic attacks) to levels approximately equal to those seen at baseline before active treatment was initiated. Rebound refers to a return of symptoms of panic disorder to a level substantially greater in frequency, or more severe in intensity than seen at baseline. Withdrawal symptoms were identified as those which were generally not characteristic of panic disorder and which occurred for the first time more frequently during discontinuation than at baseline.

In a controlled clinical trial in which 63 patients were randomized to alprazolam and where withdrawal symptoms were specifically sought, the following were identified as symptoms of withdrawal: heightened sensory perception, impaired concentration, dysosmia, clouded sensorium, paresthesias, muscle cramps, muscle twitch, diarrhea, blurred vision, appetite decrease, and weight loss. Other symptoms, such as anxiety and insomnia, were frequently seen during discontinuation, but it could not be determined if they were due to return of illness, rebound, or withdrawal.

In two controlled trials of 6 to 8 weeks duration where the ability of patients to discontinue medication was measured, 71% - 93% of patients treated with alprazolam tapered completely off therapy compared to 89% - 96% of placebo-treated patients. In a controlled postmarketing discontinuation study of panic disorder patients, the duration of treatment (3 months compared to 6 months) had no effect on the ability of patients to taper to zero dose.

Seizures attributable to alprazolam were seen after drug discontinuance or dose reduction in 8 of 1980 patients with panic disorder or in patients participating in clinical trials where doses of alprazolam greater than 4 mg/day for over 3 months were permitted. Five of these cases clearly occurred during abrupt dose reduction, or discontinuation from daily doses of 2 to 10 mg. Three cases occurred in situations where there was not a clear relationship to abrupt dose reduction or discontinuation. In one instance, seizure occurred after discontinuation from a single dose of 1 mg after tapering at a rate of 1 mg every 3 days from 6 mg daily. In two other instances, the relationship to taper is indeterminate; in both of these cases the patients had been receiving doses of 3 mg daily prior to seizure. The duration of use in the above 8 cases ranged from 4 to 22 weeks. There have been occasional voluntary reports of patients developing seizures while apparently tapering gradually from alprazolam. The risk of seizure seems to be greatest 24 - 72 hours after discontinuation (see DOSAGE AND ADMINISTRATION for recommended tapering and discontinuation schedule).

Status Epilepticus

The medical event voluntary reporting system shows that withdrawal seizures have been reported in association with the discontinuation of alprazolam. In most cases, only a single seizure was reported; however, multiple seizures and status epilepticus were reported as well.

Interdose Symptoms

Early morning anxiety and emergence of anxiety symptoms between doses of alprazolam have been reported in patients with panic disorder taking prescribed maintenance doses of alprazolam. These symptoms may reflect the development of tolerance or a time interval between doses which is longer than the duration of clinical action of the administered dose. In either case, it is presumed that the prescribed dose is not sufficient to maintain plasma levels above those needed to prevent relapse, rebound or withdrawal symptoms over the entire course of the interdosing interval. In these situations, it is recommended that the same total daily dose be given divided as more frequent administrations (see DOSAGE AND ADMINISTRATION).

Risk of Dose Reduction

Withdrawal reactions may occur when dosage reduction occurs for any reason. This includes purposeful tapering, but also inadvertent reduction of dose (eg, the patient forgets, the patient is admitted to a hospital). Therefore, the dosage of NIRAVAM® should be reduced or discontinued gradually (see DOSAGE AND ADMINISTRATION).

CNS Depression and Impaired Performance

Because of its CNS depressant effects, patients receiving alprazolam should be cautioned against engaging in hazardous occupations or activities requiring complete mental alertness such as operating machinery or driving a motor vehicle. For the same reason, patients should be cautioned about the simultaneous ingestion of alcohol and other CNS depressant drugs during treatment with alprazolam.

Risk of Fetal Harm

Benzodiazepines can potentially cause fetal harm when administered to pregnant women. If alprazolam is used during pregnancy, or if the patient becomes pregnant while taking this drug, the patient should be apprised of the potential hazard to the fetus. Because of experience with other members of the benzodiazepine class, alprazolam is assumed to be capable of causing an increased risk of congenital abnormalities when administered to a pregnant woman during the first trimester. Because use of these drugs is rarely a matter of urgency, their use during the first trimester should almost always be avoided. The possibility that a woman of childbearing potential may be pregnant at the time of institution of therapy should be considered. Patients should be advised that if they become pregnant during therapy or intend to become pregnant they should communicate with their physicians about the desirability of discontinuing the drug.

Alprazolam Interaction with Drugs that Inhibit Metabolism via Cytochrome P450 3A

The initial step in alprazolam metabolism is hydroxylation catalyzed by cytochrome P450 3A (CYP3A). Drugs that inhibit this metabolic pathway may have a profound effect on the clearance of alprazolam. Consequently, alprazolam should be avoided in patients receiving very potent inhibitors of CYP3A. With drugs inhibiting CYP3A to a lesser but still significant degree, alprazolam should be used only with caution and consideration of appropriate dosage reduction. For some drugs, an interaction with alprazolam has been quantified with clinical data; for other drugs, interactions are predicted from in vitro data and/or experience with similar drugs in the same pharmacologic class.

The following are examples of drugs known to inhibit the metabolism of alprazolam and/or related benzodiazepines, presumably through inhibition of CYP3A.

Potent CYP3A Inhibitors

Azole antifungal agents— Ketoconazole and itraconazole are potent CYP3A inhibitors and have been shown in vivo to increase plasma alprazolam concentrations 3.98 fold and 2.70 fold, respectively. The coadministration of alprazolam with these agents is not recommended. Other azole-type antifungal agents should also be considered potent CYP3A inhibitors and the coadministration of alprazolam with them is not recommended (see CONTRAINDICATIONS).

Drugs demonstrated to be CYP3A inhibitors on the basis of clinical studies involving alprazolam (caution and consideration of appropriate alprazolam dose reduction are recommended during coadministration with the following drugs)

Nefazodone — Coadministration of nefazodone increased alprazolam concentration two-fold.

Fluvoxamine — Coadministration of fluvoxamine approximately doubled the maximum plasma concentration of alprazolam, decreased clearance by 49%, increased half-life by 71%, and decreased measured psychomotor performance.

Cimetidine — Coadministration of cimetidine increased the maximum plasma concentration of alprazolam by 86%, decreased clearance by 42%, and increased half-life by 16%.

Other drugs possibly affecting alprazolam metabolism by inhibition of CYP3A are discussed in the PRECAUTIONS section (see PRECAUTIONS–Drug Interactions).

PRECAUTIONS

General

Suicide

As with other psychotropic medications, the usual precautions with respect to administration of the drug and size of the prescription are indicated for severely depressed patients or those in whom there is reason to expect concealed suicidal ideation or plans. Panic disorder has been associated with primary and secondary major depressive disorders and increased reports of suicide among untreated patients.

Mania

Episodes of hypomania and mania have been reported in association with the use of alprazolam in patients with depression.

Uricosuric Effect

Alprazolam has a weak uricosuric effect. Although other medications with weak uricosuric effect have been reported to cause acute renal failure, there have been no reported instances of acute renal failure attributable to therapy with alprazolam.

Use in Patients with Concomitant Illness

It is recommended that the dosage be limited to the smallest effective dose to preclude the development of ataxia or oversedation which may be a particular problem in elderly or debilitated patients. (See DOSAGE AND ADMINISTRATION.) The usual precautions in treating patients with impaired renal, hepatic or pulmonary function should be observed. There have been rare reports of death in patients with severe pulmonary disease shortly after the initiation of treatment with alprazolam. A decreased systemic alprazolam elimination rate (eg, increased plasma half-life) has been observed in both alcoholic liver disease patients and obese patients receiving alprazolam (see CLINICAL PHARMACOLOGY).

Information for Patients

For all users of NIRAVAM®

To assure safe and effective use of benzodiazepines, all patients prescribed NIRAVAM® should be provided with the following guidance.

1. Do not remove NIRAVAM® tablets from the bottle until just prior to dosing. With dry hands, open the bottle, remove the tablet, and immediately place on the tongue to dissolve and be swallowed with the saliva. The tablet may also be taken with water.
2. Discard any cotton that was included in the bottle and reseal the bottle tightly to prevent introducing moisture that might cause the tablets to disintegrate.
3. Store away from moisture.
4. Inform your physician about any alcohol consumption and medicine you are taking now, including medication you may buy without a prescription. Alcohol should generally not be used during treatment with benzodiazepines.
5. Not recommended for use in pregnancy. Therefore, inform your physician if you are pregnant, if you are planning to have a child, or if you become pregnant while you are taking this medication.
6. Inform your physician if you are nursing.
7. Until you experience how this medication affects you, do not drive a car or operate potentially dangerous machinery, etc.
8. Do not increase the dose even if you think the medication "does not work anymore" without consulting your physician. Benzodiazepines, even when used as recommended, may produce emotional and/or physical dependence.
9. Do not stop taking this medication abruptly or decrease the dose without consulting your physician, since withdrawal symptoms can occur.

Additional advice for panic disorder patients

The use of alprazolam at doses greater than 4 mg/day, often necessary to treat panic disorder, is accompanied by risks that you need to carefully consider. When used at doses greater than
4 mg/day, which may or may not be required for your treatment, alprazolam has the potential to cause severe emotional and physical dependence in some patients and these patients may find it exceedingly difficult to terminate treatment. In two controlled trials of 6 to 8 weeks duration where the ability of patients to discontinue medication was measured, 7 to 29% of patients treated with alprazolam did not completely taper off therapy. In a controlled postmarketing discontinuation study of panic disorder patients, the patients treated with doses of alprazolam greater than 4 mg/day had more difficulty tapering to zero dose than patients treated with less than 4 mg/day. In all cases, it is important that your physician help you discontinue this medication in a careful and safe manner to avoid overly extended use of alprazolam.

In addition, the extended use at doses greater than 4 mg/day appears to increase the incidence and severity of withdrawal reactions when alprazolam is discontinued. These are generally minor but seizure can occur, especially if you reduce the dose too rapidly or discontinue the medication abruptly. Seizure can be life-threatening.

Laboratory Tests

Laboratory tests are not ordinarily required in otherwise healthy patients. However, when treatment is protracted, periodic blood counts, urinalysis, and blood chemistry analyses are advisable in keeping with good medical practice.

Drug Interactions

Use with Other CNS Depressants

If NIRAVAM® is to be combined with other psychotropic agents or anticonvulsant drugs, careful consideration should be given to the pharmacology of the agents to be employed, particularly with compounds which might potentiate the action of benzodiazepines. The benzodiazepines, including alprazolam, produce additive CNS depressant effects when co-administered with other psychotropic medications, anticonvulsants, antihistaminics, ethanol and other drugs which themselves produce CNS depression.

Drugs Effecting Salivary Flow and Stomach pH

Because NIRAVAM® disintegrates in the presence of saliva and the formulation requires an acidic environment to dissolve, concomitant drugs or diseases that cause dry mouth or raise stomach pH might slow disintegration or dissolution, resulting in slowed or decreased absorption.

Use with Imipramine and Desipramine

The steady state plasma concentrations of imipramine and desipramine have been reported to be increased an average of 31% and 20%, respectively, by the concomitant administration of alprazolam in doses up to 4 mg/day. The clinical significance of these changes is unknown.

Drugs that inhibit alprazolam metabolism via cytochrome P450 3A

The initial step in alprazolam metabolism is hydroxylation catalyzed by cytochrome P450 3A (CYP3A). Drugs which inhibit this metabolic pathway may have a profound effect on the clearance of alprazolam (see CONTRAINDICATIONS and WARNINGS for additional drugs of this type).

Drugs demonstrated to be CYP3A inhibitors of possible clinical significance on the basis of clinical studies involving alprazolam (caution is recommended during coadministration with alprazolam)

Fluoxetine — Coadministration of fluoxetine with alprazolam increased the maximum plasma concentration of alprazolam by 46%, decreased clearance by 21%, increased half-life by 17%, and decreased measured psychomotor performance.

Propoxyphene — Coadministration of propoxyphene decreased the maximum plasma concentration of alprazolam by 6%, decreased clearance by 38%, and increased half-life by 58%.

Oral Contraceptives — Coadministration of oral contraceptives increased the maximum plasma concentration of alprazolam by 18%, decreased clearance by 22%, and increased half-life by 29%.

Drugs and other substances demonstrated to be CYP3A inhibitors on the basis of clinical studies involving benzodiazepines metabolized similarly to alprazolam or on the basis of in vitro studies with alprazolam or other benzodiazepines (caution is recommended during coadministration with alprazolam)

Available data from clinical studies of benzodiazepines other than alprazolam suggest a possible drug interaction with alprazolam for the following: diltiazem, isoniazid, macrolide antibiotics such as erythromycin and clarithromycin, and grapefruit juice. Data from in vitro studies of alprazolam suggest a possible drug interaction with alprazolam for the following: sertraline and paroxetine. However, data from an in vivo drug interaction study involving a single dose of alprazolam 1 mg and steady state doses of sertraline (50 to 150 mg/day) did not reveal any clinically significant changes in the pharmacokinetics of alprazolam. Data from in vitro studies of benzodiazepines other than alprazolam suggest a possible drug interaction for the following: ergotamine, cyclosporine, amiodarone, nicardipine, and nifedipine. Caution is recommended during the coadministration of any of these with alprazolam (see WARNINGS).

Drugs demonstrated to be inducers of CYP3A

Carbamazepine can increase alprazolam metabolism and therefore can decrease plasma levels of alprazolam.

Drug/Laboratory Test Interactions

Although interactions between benzodiazepines and commonly employed clinical laboratory tests have occasionally been reported, there is no consistent pattern for a specific drug or specific test.

Carcinogenesis, Mutagenesis, Impairment of Fertility

No evidence of carcinogenic potential was observed during 2-year bioassay studies of alprazolam in rats at doses up to 30 mg/kg/day (150 times the maximum recommended daily human dose of 10 mg/day) and in mice at doses up to 10 mg/kg/day (50 times the maximum recommended daily human dose).

Alprazolam was not mutagenic in the rat micronucleus test at doses up to 100 mg/kg, which is 500 times the maximum recommended daily human dose of 10 mg/day. Alprazolam also was not mutagenic in vitro in the DNA Damage/Alkaline Elution Assay or the Ames Assay.

Alprazolam produced no impairment of fertility in rats at doses up to 5 mg/kg/day, which is
25 times the maximum recommended daily human dose of 10 mg/day.

Pregnancy

Teratogenic Effects

Pregnancy Category D

(See WARNINGS section).

Nonteratogenic Effects

It should be considered that the child born of a mother who is receiving benzodiazepines may be at some risk for withdrawal symptoms from the drug during the postnatal period. Also, neonatal flaccidity and respiratory problems have been reported in children born of mothers who have been receiving benzodiazepines.

Labor and Delivery

NIRAVAM® has no established use in labor or delivery.

Nursing Mothers

Benzodiazepines are known to be excreted in human milk. It should be assumed that alprazolam is as well. Chronic administration of diazepam to nursing mothers has been reported to cause their infants to become lethargic and to lose weight. As a general rule, nursing should not be undertaken by mothers who must use NIRAVAM®.

Pediatric Use

Safety and effectiveness of NIRAVAM® in individuals below 18 years of age have not been established.

Geriatric Use

The elderly may be more sensitive to the effects of benzodiazepines. They exhibit higher plasma alprazolam concentrations due to reduced clearance of the drug as compared with a younger population receiving the same doses. The smallest effective dose of NIRAVAM® should be used in the elderly to preclude the development of ataxia and oversedation (see CLINICAL PHARMACOLOGY and DOSAGE AND ADMINISTRATION).

ADVERSE REACTIONS

Side effects to alprazolam, if they occur, are generally observed at the beginning of therapy and usually disappear upon continued medication. In the usual patient, the most frequent side effects are likely to be an extension of the pharmacological activity of alprazolam, eg, drowsiness or lightheadedness.

The data cited in the two tables below are estimates of untoward clinical event incidence among patients who participated under the following clinical conditions: relatively short duration (ie, four weeks) placebo-controlled clinical studies with dosages up to 4 mg/day of alprazolam (for the management of anxiety disorders or for the short-term relief of the symptoms of anxiety) and short-term (up to ten weeks) placebo-controlled clinical studies with dosages up to 10 mg/day of alprazolam in patients with panic disorder, with or without agoraphobia.

These data cannot be used to predict precisely the incidence of untoward events in the course of usual medical practice where patient characteristics, and other factors often differ from those in clinical trials. These figures cannot be compared with those obtained from other clinical studies involving related drug products and placebo as each group of drug trials are conducted under a different set of conditions.

Comparison of the cited figures, however, can provide the prescriber with some basis for estimating the relative contributions of drug and non-drug factors to the untoward event incidence in the population studied. Even this use must be approached cautiously, as a drug may relieve a symptom in one patient but induce it in others. (For example, an anxiolytic drug may relieve dry mouth [a symptom of anxiety] in some subjects but induce it [an untoward event] in others.)

Additionally, for anxiety disorders the cited figures can provide the prescriber with an indication as to the frequency with which physician intervention (eg, increased surveillance, decreased dosage or discontinuation of drug therapy) may be necessary because of the untoward clinical event.

Treatment-Emergent Adverse Events Reported in Placebo-Controlled Trials of Anxiety Disorders
 | ANXIETY DISORDERS
 | Treatment-Emergent Symptom Incidence [Events reported by 1% or more of alprazolam patients are included.] |  | Incidence of Intervention Because of Symptom
 | ALPRAZOLAM | PLACEBO | ALPRAZOLAM
Number of Patients; % of Patients; Reporting: | 565 | 505 | 565
Central Nervous System
Drowsiness | 41.0 | 21.6 | 15.1
Lightheadedness | 20.8 | 19.3 | 1.2
Depression | 13.9 | 18.1 | 2.4
Headache | 12.9 | 19.6 | 1.1
Confusion | 9.9 | 10.0 | 0.9
Insomnia | 8.9 | 18.4 | 1.3
Nervousness | 4.1 | 10.3 | 1.1
Syncope | 3.1 | 4.0 | [None reported]
Dizziness | 1.8 | 0.8 | 2.5
Akathisia | 1.6 | 1.2
Tiredness/Sleepiness |  |  | 1.8
Gastrointestinal
Dry Mouth | 14.7 | 13.3 | 0.7
Constipation | 10.4 | 11.4 | 0.9
Diarrhea | 10.1 | 10.3 | 1.2
Nausea/Vomiting | 9.6 | 12.8 | 1.7
Increased Salivation | 4.2 | 2.4
Cardiovascular
Tachycardia/Palpitations | 7.7 | 15.6 | 0.4
Hypotension | 4.7 | 2.2
Sensory
Blurred Vision | 6.2 | 6.2 | 0.4
Musculoskeletal
Rigidity | 4.2 | 5.3
Tremor | 4.0 | 8.8 | 0.4
Cutaneous
Dermatitis/Allergy | 3.8 | 3.1 | 0.6
Other
Nasal Congestion | 7.3 | 9.3
Weight Gain | 2.7 | 2.7
Weight Loss | 2.3 | 3.0

In addition to the relatively common (ie, greater than 1%) untoward events enumerated in the table above, the following adverse events have been reported in association with the use of benzodiazepines: dystonia, irritability, concentration difficulties, anorexia, transient amnesia or memory impairment, loss of coordination, fatigue, seizures, sedation, slurred speech, jaundice, musculoskeletal weakness, pruritus, diplopia, dysarthria, changes in libido, menstrual irregularities, incontinence and urinary retention.

Treatment-Emergent Adverse Events Reported in Placebo-Controlled Trials of Panic Disorder
PANIC DISORDER
 | Treatment-Emergent Symptom Incidence
 | ALPRAZOLAM | PLACEBO
Number of Patients % of Patients Reporting: | 1388 | 1231
Central Nervous System
Drowsiness | 76.8 | 42.7
Fatigue and Tiredness | 48.6 | 42.3
Impaired Coordination | 40.1 | 17.9
Irritability | 33.1 | 30.1
Memory Impairment | 33.1 | 22.1
Lightheadedness/Dizziness | 29.8 | 36.9
Insomnia | 29.4 | 41.8
Headache | 29.2 | 35.6
Cognitive Disorder | 28.8 | 20.5
Dysarthria | 23.3 | 6.3
Anxiety | 16.6 | 24.9
Abnormal Involuntary Movement | 14.8 | 21.0
Decreased Libido | 14.4 | 8.0
Depression | 13.8 | 14.0
Confusional State | 10.4 | 8.2
Muscular Twitching | 7.9 | 11.8
Increased Libido | 7.7 | 4.1
Change in Libido (Not Specified) | 7.1 | 5.6
Weakness | 7.1 | 8.4
Muscle Tone Disorders | 6.3 | 7.5
Syncope | 3.8 | 4.8
Akathisia | 3.0 | 4.3
Agitation | 2.9 | 2.6
Disinhibition | 2.7 | 1.5
Paresthesia | 2.4 | 3.2
Talkativeness | 2.2 | 1.0
Vasomotor Disturbances | 2.0 | 2.6
Derealization | 1.9 | 1.2
Dream Abnormalities | 1.8 | 1.5
Fear | 1.4 | 1.0
Feeling Warm | 1.3 | 0.5
Gastrointestinal
Decreased Salivation | 32.8 | 34.2
Constipation | 26.2 | 15.4
Nausea/Vomiting | 22.0 | 31.8
Diarrhea | 20.6 | 22.8
Abdominal Distress | 18.3 | 21.5
Increased Salivation | 5.6 | 4.4
Cardio-Respiratory
Nasal Congestion | 17.4 | 16.5
Tachycardia | 15.4 | 26.8
Chest Pain | 10.6 | 18.1
Hyperventilation | 9.7 | 14.5
Upper Respiratory Infection | 4.3 | 3.7
Sensory
Blurred Vision | 21.0 | 21.4
Tinnitus | 6.6 | 10.4
Musculoskeletal
Muscular Cramps | 2.4 | 2.4
Muscle Stiffness | 2.2 | 3.3
Cutaneous
Sweating | 15.1 | 23.5
Rash | 10.8 | 8.1
Other
Increased Appetite | 32.7 | 22.8
Decreased Appetite | 27.8 | 24.1
Weight Gain | 27.2 | 17.9
Weight Loss | 22.6 | 16.5
Micturition Difficulties | 12.2 | 8.6
Menstrual Disorders | 10.4 | 8.7
Sexual Dysfunction | 7.4 | 3.7
Edema | 4.9 | 5.6
Incontinence | 1.5 | 0.6
Infection | 1.3 | 1.7

In addition to the relatively common (ie, greater than 1%) untoward events enumerated in the table above, the following adverse events have been reported in association with the use of alprazolam: seizures, hallucinations, depersonalization, taste alterations, diplopia, elevated bilirubin, elevated hepatic enzymes, and jaundice.

Panic disorder has been associated with primary and secondary major depressive disorders and increased reports of suicide among untreated patients (see PRECAUTIONS, General).

Adverse Events Reported as Reasons for Discontinuation in Treatment of Panic Disorder in Placebo-Controlled Trials

In a larger database comprised of both controlled and uncontrolled studies in which 641 patients received alprazolam, discontinuation-emergent symptoms which occurred at a rate of over 5% in patients treated with alprazolam and at a greater rate than the placebo-treated group were as follows:

DISCONTINUATION-EMERGENT SYMPTOM INCIDENCE
Percentage of 641 Alprazolam-Treated Panic Disorder
Patients Reporting Events
Body System/Event
Neurologic |  | Gastrointestinal
Insomnia | 29.5 | Nausea/Vomiting | 16.5
Lightheadedness | 19.3 | Diarrhea | 13.6
Abnormal involuntary movement | 17.3 | Decreased salivation | 10.6
Headache | 17.0
Muscular twitching | 6.9 | Metabolic-Nutritional
Impaired coordination | 6.6 | Weight loss | 13.3
Muscle tone disorders | 5.9 | Decreased appetite | 12.8
Weakness | 5.8
 |  | Dermatological
Psychiatric |  | Sweating | 14.4
Anxiety | 19.2
Fatigue and Tiredness | 18.4 | Cardiovascular
Irritability | 10.5 | Tachycardia | 12.2
Cognitive Disorder | 10.3
Memory Impairment | 5.5 | Special Senses
Depression | 5.1 | Blurred vision | 10.0
Confusional state | 5.0

From the studies cited, it has not been determined whether these symptoms are clearly related to the dose and duration of therapy with alprazolam in patients with panic disorder. There have also been reports of withdrawal seizures upon rapid decrease or abrupt discontinuation of alprazolam (see WARNINGS).

To discontinue treatment in patients taking NIRAVAM®, the dosage should be reduced slowly in keeping with good medical practice. It is suggested that the daily dosage of NIRAVAM® be decreased by no more than 0.5 mg every three days (see DOSAGE AND ADMINISTRATION). Some patients may benefit from an even slower dosage reduction. In a controlled postmarketing discontinuation study of panic disorder patients which compared this recommended taper schedule with a slower taper schedule, no difference was observed between the groups in the proportion of patients who tapered to zero dose; however, the slower schedule was associated with a reduction in symptoms associated with a withdrawal syndrome.

As with all benzodiazepines, paradoxical reactions such as stimulation, increased muscle spasticity, sleep disturbances, hallucinations and other adverse behavioral effects such as agitation, rage, irritability, and aggressive or hostile behavior have been reported rarely. In many of the spontaneous case reports of adverse behavioral effects, patients were receiving other CNS drugs concomitantly and/or were described as having underlying psychiatric conditions. Should any of the above events occur, alprazolam should be discontinued. Isolated published reports involving small numbers of patients have suggested that patients who have borderline personality disorder, a prior history of violent or aggressive behavior, or alcohol or substance abuse may be at risk for such events. Instances of irritability, hostility, and intrusive thoughts have been reported during discontinuation of alprazolam in patients with posttraumatic stress disorder.

Post Introduction Reports: Various adverse drug reactions have been reported in association with the use of alprazolam since market introduction. The majority of these reactions were reported through the medical event voluntary reporting system. Because of the spontaneous nature of the reporting of medical events and the lack of controls, a causal relationship to the use of alprazolam cannot be readily determined. Reported events include: liver enzyme elevations, hepatitis, hepatic failure, Stevens-Johnson syndrome, hyperprolactinemia, gynecomastia, and galactorrhea.

DRUG ABUSE AND DEPENDENCE

Physical and Psychological Dependence

Withdrawal symptoms similar in character to those noted with sedative/hypnotics and alcohol have occurred following discontinuance of benzodiazepines, including alprazolam. The symptoms can range from mild dysphoria and insomnia to a major syndrome that may include abdominal and muscle cramps, vomiting, sweating, tremors and convulsions. Distinguishing between withdrawal emergent signs and symptoms and the recurrence of illness is often difficult in patients undergoing dose reduction. The long term strategy for treatment of these phenomena will vary with their cause and the therapeutic goal. When necessary, immediate management of withdrawal symptoms requires re-institution of treatment at doses of alprazolam sufficient to suppress symptoms. There have been reports of failure of other benzodiazepines to fully suppress these withdrawal symptoms. These failures have been attributed to incomplete cross-tolerance but may also reflect the use of an inadequate dosing regimen of the substituted benzodiazepine or the effects of concomitant medications.

While it is difficult to distinguish withdrawal and recurrence for certain patients, the time course and the nature of the symptoms may be helpful. A withdrawal syndrome typically includes the occurrence of new symptoms, tends to appear toward the end of taper or shortly after discontinuation, and will decrease with time. In recurring panic disorder, symptoms similar to those observed before treatment may recur either early or late, and they will persist.

While the severity and incidence of withdrawal phenomena appear to be related to dose and duration of treatment, withdrawal symptoms, including seizures, have been reported after only brief therapy with alprazolam at doses within the recommended range for the treatment of anxiety (eg, 0.75 to 4 mg/day). Signs and symptoms of withdrawal are often more prominent after rapid decrease of dosage or abrupt discontinuance. The risk of withdrawal seizures may be increased at doses above 4 mg/day (see WARNINGS).

Patients, especially individuals with a history of seizures or epilepsy, should not be abruptly discontinued from any CNS depressant agent, including alprazolam. It is recommended that all patients on NIRAVAM® who require a dosage reduction be gradually tapered under close supervision (see WARNINGS and DOSAGE AND ADMINISTRATION).

Psychological dependence is a risk with all benzodiazepines, including NIRAVAM®. The risk of psychological dependence may also be increased at doses greater than 4 mg/day and with longer term use, and this risk is further increased in patients with a history of alcohol or drug abuse. Some patients have experienced considerable difficulty in tapering and discontinuing from alprazolam, especially those receiving higher doses for extended periods. Addiction-prone individuals should be under careful surveillance when receiving NIRAVAM®. As with all anxiolytics, repeat prescriptions should be limited to those who are under medical supervision.

Controlled Substance Class

Alprazolam is a controlled substance under the Controlled Substance Act by the Drug Enforcement Administration and NIRAVAM® has been assigned to Schedule IV.

OVERDOSAGE

Clinical Experience

Manifestations of alprazolam overdosage include somnolence, confusion, impaired coordination, diminished reflexes and coma. Death has been reported in association with overdoses of alprazolam by itself, as it has with other benzodiazepines. In addition, fatalities have been reported in patients who have overdosed with a combination of a single benzodiazepine, including alprazolam, and alcohol; alcohol levels seen in some of these patients have been lower than those usually associated with alcohol-induced fatality.

The acute oral LD50 in rats is 331 - 2171 mg/kg. Other experiments in animals have indicated that cardiopulmonary collapse can occur following massive intravenous doses of alprazolam (over 195 mg/kg; 975 times the maximum recommended daily human dose of 10 mg/day). Animals could be resuscitated with positive mechanical ventilation and the intravenous infusion of norepinephrine bitartrate.

Animal experiments have suggested that forced diuresis or hemodialysis are probably of little value in treating overdosage.

General Treatment of Overdose

Overdosage reports with alprazolam are limited. As in all cases of drug overdosage, respiration, pulse rate, and blood pressure should be monitored. General supportive measures should be employed, along with immediate gastric lavage. Intravenous fluids should be administered and an adequate airway maintained. If hypotension occurs, it may be combated by the use of vasopressors. Dialysis is of limited value. As with the management of intentional overdosing with any drug, it should be borne in mind that multiple agents may have been ingested.

Flumazenil, a specific benzodiazepine receptor antagonist, is indicated for the complete or partial reversal of the sedative effects of benzodiazepines and may be used in situations when an overdose with a benzodiazepine is known or suspected. Prior to the administration of flumazenil, necessary measures should be instituted to secure airway, ventilation and intravenous access. Flumazenil is intended as an adjunct to, not as a substitute for, proper management of benzodiazepine overdose. Patients treated with flumazenil should be monitored for re-sedation, respiratory depression, and other residual benzodiazepine effects for an appropriate period after treatment. The prescriber should be aware of a risk of seizure in association with flumazenil treatment, particularly in long-term benzodiazepine users and in cyclic antidepressant overdose. The complete flumazenil package insert including CONTRAINDICATIONS, WARNINGS and PRECAUTIONS should be consulted prior to use.

DOSAGE AND ADMINISTRATION

Dosage should be individualized for maximum beneficial effect. While the usual daily dosages given below will meet the needs of most patients, there will be some who require doses greater than 4 mg/day. In such cases, dosage should be increased cautiously to avoid adverse effects.

Anxiety Disorders and Transient Symptoms of Anxiety

Treatment for patients with anxiety should be initiated with a dose of 0.25 to 0.5 mg given three times daily. The dose may be increased to achieve a maximum therapeutic effect, at intervals of
3 to 4 days, to a maximum daily dose of 4 mg, given in divided doses. The lowest possible effective dose should be employed and the need for continued treatment reassessed frequently. The risk of dependence may increase with dose and duration of treatment.

In all patients, dosage should be reduced gradually when discontinuing therapy or when decreasing the daily dosage. Although there are no systematically collected data to support a specific discontinuation schedule, it is suggested that the daily dosage be decreased by no more than 0.5 mg every 3 days. Some patients may require an even slower dosage reduction.

Panic Disorder

The successful treatment of many panic disorder patients has required the use of alprazolam at doses greater than 4 mg daily. In controlled trials conducted to establish the efficacy of alprazolam in panic disorder, doses in the range of 1 to 10 mg daily were used. The mean dosage employed was approximately 5 to 6 mg daily. Among the approximately 1700 patients participating in the panic disorder development program, about 300 received alprazolam in dosages of greater than 7 mg/day, including approximately 100 patients who received maximum dosages of greater than 9 mg/day. Occasional patients required as much as 10 mg a day to achieve a successful response.

Dose Titration

Treatment may be initiated with a dose of 0.5 mg three times daily. Depending on the response, the dose may be increased at intervals of 3 to 4 days in increments of no more than 1 mg per day. Slower titration to the dose levels greater than 4 mg/day may be advisable to allow full expression of the pharmacodynamic effect of alprazolam. To lessen the possibility of interdose symptoms, the times of administration should be distributed as evenly as possible throughout the waking hours, that is, on a three or four times per day schedule.

Generally, therapy should be initiated at a low dose to minimize the risk of adverse responses in patients especially sensitive to the drug. Dose should be advanced until an acceptable therapeutic response (ie, a substantial reduction in or total elimination of panic attacks) is achieved, intolerance occurs, or the maximum recommended dose is attained.

Dose Maintenance

For patients receiving doses greater than 4 mg/day, periodic reassessment and consideration of dosage reduction is advised. In a controlled postmarketing dose-response study, patients treated with doses of alprazolam greater than 4 mg/day for 3 months were able to taper to 50% of their total maintenance dose without apparent loss of clinical benefit. Because of the danger of withdrawal, abrupt discontinuation of treatment should be avoided. (See WARNINGS, PRECAUTIONS, DRUG ABUSE AND DEPENDENCE.)

The necessary duration of treatment for panic disorder patients responding to alprazolam is unknown. After a period of extended freedom from attacks, a carefully supervised tapered discontinuation may be attempted, but there is evidence that this may often be difficult to accomplish without recurrence of symptoms and/or the manifestation of withdrawal phenomena.

Dose Reduction

Because of the danger of withdrawal, abrupt discontinuation of treatment should be avoided (see WARNINGS, PRECAUTIONS, DRUG ABUSE AND DEPENDENCE).

In all patients, dosage should be reduced gradually when discontinuing therapy or when decreasing the daily dosage. Although there are no systematically collected data to support a specific discontinuation schedule, it is suggested that the daily dosage be decreased by no more than 0.5 mg every three days. Some patients may require an even slower dosage reduction.

In any case, reduction of dose must be undertaken under close supervision and must be gradual. If significant withdrawal symptoms develop, the previous dosing schedule should be reinstituted and, only after stabilization, should a less rapid schedule of discontinuation be attempted. In a controlled postmarketing discontinuation study of panic disorder patients which compared this recommended taper schedule with a slower taper schedule, no difference was observed between the groups in the proportion of patients who tapered to zero dose; however, the slower schedule was associated with a reduction in symptoms associated with a withdrawal syndrome. It is suggested that the dose be reduced by no more than 0.5 mg every 3 days, with the understanding that some patients may benefit from an even more gradual discontinuation. Some patients may prove resistant to all discontinuation regimens.

Dosing in Special Populations

In elderly patients, in patients with advanced liver disease or in patients with debilitating disease, the usual starting dose is 0.25 mg, given two or three times daily. This may be gradually increased if needed and tolerated. The elderly may be especially sensitive to the effects of benzodiazepines. If side effects occur at the recommended starting dose, the dose may be lowered.

Instructions to be Given to Patients for Use/Handling NIRAVAM® Tablets

Just prior to administration, with dry hands, remove the tablet from the bottle. Immediately place the NIRAVAM® tablet on top of the tongue where it will disintegrate, and be swallowed with saliva. Administration with liquid is not necessary.

Discard any cotton that was included in the bottle and reseal the bottle tightly to prevent introducing moisture that might cause the tablets to disintegrate.

HOW SUPPLIED

NIRAVAM® (alprazolam orally disintegrating tablets) 0.25 mg are yellow, round, orange-flavored, scored and engraved "SP 321" on the unscored side and "0.25" on the scored side. They are supplied as follows:

 | Bottles of 100 |  | NDC 0091-3321-01

NIRAVAM® (alprazolam orally disintegrating tablets) 0.5 mg are yellow, round, orange-flavored, scored and engraved "SP 322" on the unscored side and "0.5" on the scored side. They are supplied as follows:

 | Bottles of 100 |  | NDC 0091-3322-01

NIRAVAM® (alprazolam orally disintegrating tablets) 1 mg are white, round, orange-flavored, scored and engraved "SP 323" on the unscored side and "1" on the scored side. They are supplied as follows:

 | Bottles of 100 |  | NDC 0091-3323-01

NIRAVAM® (alprazolam orally disintegrating tablets) 2 mg are white, round, orange-flavored, scored and engraved "SP 324" on the unscored side and "2" on the scored side. They are supplied as follows:

 | Bottles of 100 |  | NDC 0091-3324-01

STORAGE AND HANDLING

Store at 20° to 25°C (68° to 77°F); excursions permitted between 15° to 30°C (59° to 86°F) [See USP Controlled Room Temperature]. Protect from moisture.

Dispense in a tight container as defined in the USP/NF.

ANIMAL STUDIES

When rats were treated with alprazolam at 3, 10, and 30 mg/kg/day (15 to 150 times the maximum recommended human dose) orally for 2 years, a tendency for a dose related increase in the number of cataracts was observed in females and a tendency for a dose related increase in corneal vascularization was observed in males. These lesions did not appear until after 11 months of treatment.

Manufactured for:
Schwarz
Pharma
Milwaukee, WI 53201, USA

By: CIMA LABS INC.
Eden Prairie, MN 55344, USA

NIRAVAM® uses CIMA LABS INC. U.S. Patent Nos. 6,024,981 and 6,221,392.

NIRAVAM® is a registered trademark of SRZ Properties, Inc.

PC4714D
Rev. 12/06

PACKAGE LABEL - NIRAVAM C-IV - 0.5 MG - TABS

NIRAVAM® 0.5 mg
(alprazolam orally disintegrating tablets)

Rx only

SCHWARZ
PHARMA

orally
disintegrating
tablets